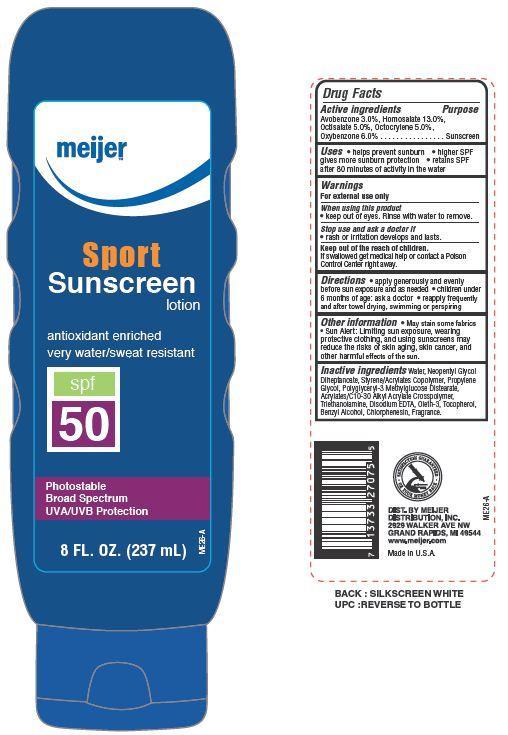 DRUG LABEL: Meijer Sport SPF 50
NDC: 41250-032 | Form: LOTION
Manufacturer: Meijer Distribution Inc
Category: otc | Type: HUMAN OTC DRUG LABEL
Date: 20130712

ACTIVE INGREDIENTS: AVOBENZONE 3 g/100 g; HOMOSALATE 13 g/100 g; OCTISALATE 5 g/100 g; OCTOCRYLENE 5 g/100 g; OXYBENZONE 6 g/100 g
INACTIVE INGREDIENTS: WATER; NEOPENTYL GLYCOL DIHEPTANOATE; PROPYLENE GLYCOL; METHANOLAMINE; EDETATE DISODIUM; OLETH-3; TOCOPHEROL; BENZYL ALCOHOL; CHLORPHENESIN

Drug Facts

Active ingredients

Avobenzone 3.0%

Homosalate 13.0%

Octisalate 5.0%

Octocrylene 5.0%

Oxybenzone 6.0%

Uses

- helps prevent suburn
- higher SPF gives more sunburn protection
- retains SPF after 80 minutes of activity in water

Warnings

For external use only

When using this product

- keep out of eyes. Rinse with water to remove

Stop use and ask a doctor if

- rash or irritation develops and lasts

KEEP OUT OF REACH OF CHILDREN

Keep out of the reach of children. If swallowed get medical help or contact a Poison Control Center right away.

Directions

- apply generously and evenly before sun exposure and as needed
- children under 6 months of age: ask a doctor
- reapply frequently and after towel drying, swimming or perspiring

Other information

- may stain some fabrics
- Sun Alert: Limiting sun exposure, wearing protective clothing, and using sunscreens may reduce the risks of skin aging, skin cancer and other harmful effects of the sun

Inactive ingredients

Water, Neopentyl Glycol Diheptanoate, Styrene/Acrylates Copolymer, Propylene Glycol, Acrylates/C12-22 Alkyl Methacrylate Copolymer, Benzyl Alcohol, Polyglyceryl-3 Methylglucose Distearate, Acrylates/C10-30 Alkyl Acrylate Crosspolymer, Triethanolamine, Disodium EDTA, Tocopherol, Oleth-3, Chlorphenesin, Fragrance.

Principal Display Panel

meijer

Sport

Sunscreen lotion

antioxidant enriched

very water/sweat resistant

spf 50

Photostable

Broad Spectrum

UVA/UVB Protection

8 FL. OZ. (237 mL)

Purpose

Sunscreen